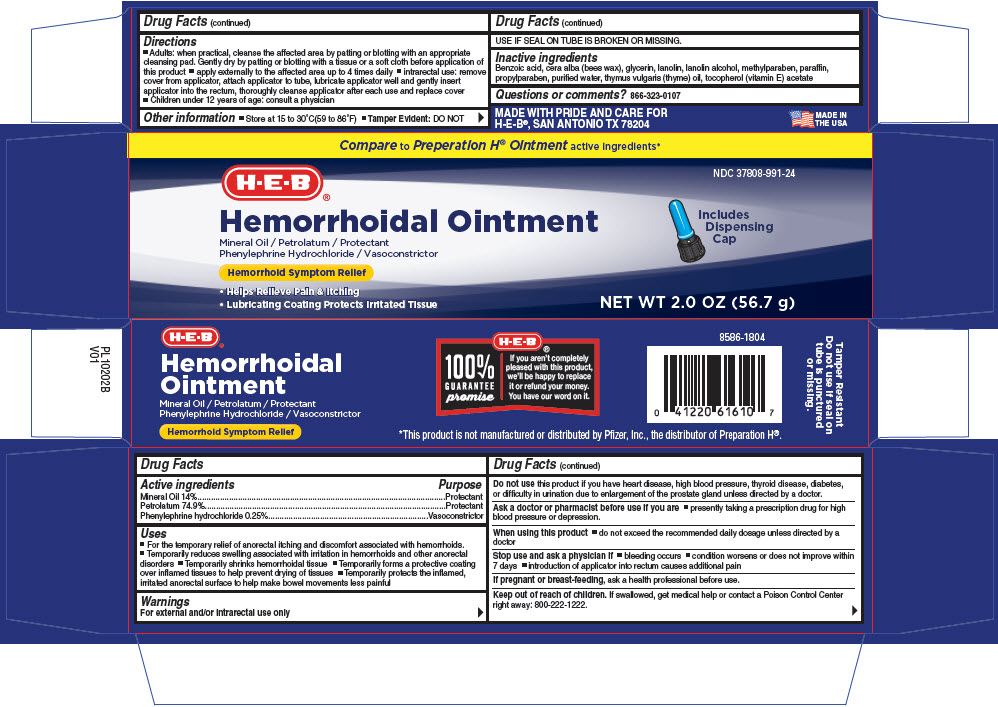 DRUG LABEL: HEB Hemorrhoidal
NDC: 37808-991 | Form: CREAM
Manufacturer: H-E-B
Category: otc | Type: HUMAN OTC DRUG LABEL
Date: 20181025

ACTIVE INGREDIENTS: Mineral Oil 14 g/100 g; Petrolatum 74.9 g/100 g; Phenylephrine Hydrochloride 0.25 g/100 g
INACTIVE INGREDIENTS: Benzoic Acid; White Wax; Glycerin; Lanolin; Lanolin Alcohols; Methylparaben; Paraffin; Propylparaben; Water; Thyme Oil; .Alpha.-Tocopherol Acetate

HEB Hemorrhoidal Ointment

Drug Facts

ACTIVE INGREDIENT

Active ingredients | Purpose
Mineral Oil 14% | Protectant
Petrolatum 74.9% | Protectant
Phenylephrine hydrochloride 0.25% | Vasoconstrictor

Uses

- For the temporary relief of anorectal itching and discomfort associated with hemorrhoids.
- Temporarily reduces swelling associated with irritation in hemorrhoids and other anorectal disorders
- Temporarily shrinks hemorrhoidal tissue
- Temporarily forms a protective coating over inflamed tissues to help prevent drying of tissues
- Temporarily protects the inflamed, irritated anorectal surface to help make bowel movements less painful

Warnings

For external and/or intrarectal use only

Do not use this product if you have heart disease, high blood pressure, thyroid disease, diabetes, or difficulty in urination due to enlargement of the prostate gland unless directed by a doctor.

Ask a doctor or pharmacist before use if you are

- presently taking a prescription drug for high blood pressure or depression.

When using this product

- do not exceed the recommended daily dosage unless directed by a doctor

Stop use and ask a physician if

- bleeding occurs
- condition worsens or does not improve within 7 days
- introduction of applicator into rectum causes additional pain

PREGNANCY OR BREAST FEEDING

If pregnant or breast-feeding, ask a health professional before use.

Keep out of reach of children. If swallowed, get medical help or contact a Poison Control Center right away: 800-222-1222.

Directions

- Adults: when practical, cleanse the affected area by patting or blotting with an appropriate cleansing pad. Gently dry by patting or blotting with a tissue or a soft cloth before application of this product
- apply externally to the affected area up to 4 times daily
- intrarectal use: remove cover from applicator, attach applicator to tube, lubricate applicator well and gently insert applicator into the rectum, thoroughly cleanse applicator after each use and replace cover
- Children under 12 years of age: consult a physician

Other information

- Store at 15 to 30°C(59 to 86°F)
- Tamper Evident: DO NOT USE IF SEAL ON TUBE IS BROKEN OR MISSING.

Inactive ingredients

Benzoic acid, cera alba (bees wax), glycerin, lanolin, lanolin alcohol, methylparaben, paraffin, propylparaben, purified water, thymus vulgaris (thyme) oil, tocopherol (vitamin E) acetate

Questions or comments?

866-323-0107

PRINCIPAL DISPLAY PANEL - 56.7 g Tube Carton

Compare to Preperation H® Ointment active ingredients*

H-E-B ®

NDC 37808-991-24

Hemorrhoidal Ointment
Mineral Oil / Petrolatum / Protectant
Phenylephrine Hydrochloride / Vasoconstrictor

Includes
Dispensing
Cap

Hemorrhoid Symptom Relief

- Helps Relieve Pain & Itching
- Lubricating Coating Protects Irritated Tissue

NET WT 2.0 OZ (56.7 g)